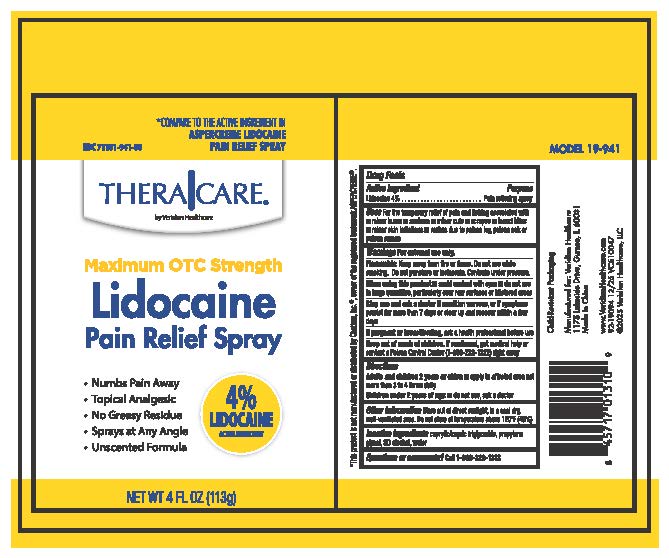 DRUG LABEL: TheraCare Lidocaine  Pain Relief
NDC: 71101-941 | Form: SPRAY
Manufacturer: Veridian Healthcare
Category: otc | Type: HUMAN OTC DRUG LABEL
Date: 20260105

ACTIVE INGREDIENTS: LIDOCAINE 4 mg/1 mL
INACTIVE INGREDIENTS: ALCOHOL 95%; WATER; CAPRYLIC/CAPRIC TRIGLYCERIDE; PROPYLENE GLYCOL

TheraCare Lidocaine Pain Relief Spray

Active ingredient

Lidocaine 4%

Purpose

Pain relieving spray

Uses

Uses For the temporary relief of minor aches and pain associated with

• minor burns

- sunburn
- minor cuts
- scrapes
- insect bites
- minor skin irritations
- rashes due to poison ivy, poison oak or poison sumac

Warnings

For external use only.

Flammable.Keep away from fire or flame. Do not use while smoking. Do not punture or incinerate. Contents under pressure

When using this product

- Avoid contact with eyes.
- do not use in large quatities, particularly over raw surfaces or blistered areas

Stop use and ask a doctor if

- condition worsens
- or if symptoms persist for more than 7 days or clear up and reoccur within a few days

Keep out of reach of children.

If swallowed, get medical help or contact a Poison Control Center (1-800-222-1222) right away

If pregnant or breastfeeding

Ask a helth professional before use

Directions

Adults and children 2 years or older:Apply to affected area not more than 3 to 4 times daily. Children under 2 years of age: do not use, ask a doctor.

Other information

Store out of direct sunlight, in a cool dry, well-ventilated area. Do not store at temperature above 120F (49C)

Inactive ingredients

caprylic/capric triglyceride, propylene glycol, SD alcohol, water

Questions or comments?

1-888-326-1313